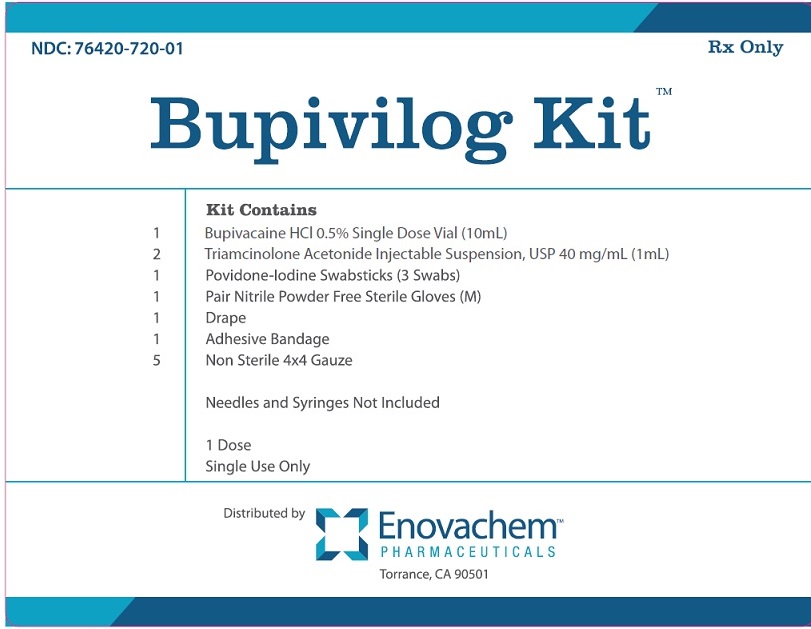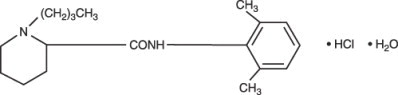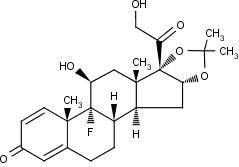 DRUG LABEL: Bupivilog Kit
NDC: 76420-720 | Form: KIT | Route: EPIDURAL
Manufacturer: Asclemed USA, Inc.
Category: prescription | Type: HUMAN PRESCRIPTION DRUG LABEL
Date: 20260108

ACTIVE INGREDIENTS: BUPIVACAINE HYDROCHLORIDE 5 mg/1 mL; TRIAMCINOLONE ACETONIDE 40 mg/1 mL; POVIDONE-IODINE 10 mg/1 mL
INACTIVE INGREDIENTS: SODIUM CHLORIDE 8.1 mg/1 mL; SODIUM HYDROXIDE; HYDROCHLORIC ACID; WATER; SODIUM CHLORIDE; BENZYL ALCOHOL; CARBOXYMETHYLCELLULOSE SODIUM; POLYSORBATE 80; SODIUM HYDROXIDE; HYDROCHLORIC ACID; NITROGEN; NONOXYNOL-9; WATER

HIGHLIGHTS OF PRESCRIBING INFORMATION

These highlights do not include all the information needed to use BUPIVACAINE HYDROCHLORIDE INJECTION safely and effectively. See full prescribing information for BUPIVACAINE HYDROCHLORIDE INJECTION.
BUPIVACAINE HYDROCHLORIDE injection, for infiltration, perineural, caudal, epidural, or retrobulbar use
Initial U.S. Approval: 1972

WARNING: RISK OF CARDIAC ARREST WITH USE OF BUPIVACAINE HYDROCHLORIDE INJECTION IN OBSTETRICAL ANESTHESIA

See full prescribing information for complete boxed warning.

There have been reports of cardiac arrest with difficult resuscitation or death during use of Bupivacaine Hydrochloride Injection for epidural anesthesia in obstetrical patients. In most cases, this has followed use of the 0.75% (7.5 mg/mL) concentration. Resuscitation has been difficult or impossible despite apparently adequate preparation and appropriate management. Cardiac arrest has occurred after convulsions resulting from systemic toxicity, presumably following unintentional intravascular injection. The 0.75% (7.5 mg/mL) concentration of Bupivacaine Hydrochloride Injection is not recommended for obstetrical anesthesia and should be reserved for surgical procedures where a high degree of muscle relaxation and prolonged effect are necessary (5.1).

1 INDICATIONS AND USAGE

Bupivacaine Hydrochloride Injection contains bupivacaine, an amide local anesthetic. Bupivacaine Hydrochloride Injection is indicated in adults for the production of local or regional anesthesia or analgesia for surgery, dental and oral surgery procedures, diagnostic and therapeutic procedures, and for obstetrical procedures. For each type of block indicated to produce local or regional anesthesia or analgesia, specific concentrations and presentations are recommended. (1, 2.2)

Limitations of Use

Not all blocks are indicated for use with Bupivacaine Hydrochloride Injection given clinically significant risks associated with use. (1, 2.2, 4, 5.1, 5.5, 5.7, 5.9)

2 DOSAGE AND ADMINISTRATION

- Not for intrathecal use. (2.1)
- Avoid use of solutions containing antimicrobial preservatives (i.e., multiple-dose vials) for epidural or caudal anesthesia. (2.1)
- See full prescribing information for:

- Recommended concentrations and dosages of Bupivacaine Hydrochloride Injection according to type of block. (2.2)

- Additional dosage and administration information pertaining to use in epidural anesthesia and use in ophthalmic surgery. (2.3, 2.6)

3 DOSAGE FORMS AND STRENGTHS

Bupivacaine Hydrochloride Injection, USP are available in following concentrations. See full prescribing information for detailed description of each formulation. (3)

4 CONTRAINDICATIONS

- Obstetrical paracervical block anesthesia. Its use in this technique has resulted in fetal bradycardia and death. (4)
- Intravenous regional anesthesia (Bier Block). (4)
- Known hypersensitivity to bupivacaine or to any local anesthetic agent of the amide-type or to other components of Bupivacaine Hydrochloride Injection. (4)

5 WARNINGS AND PRECAUTIONS

- Dose-Related Toxicity: Monitor cardiovascular and respiratory vital signs and patient's state of consciousness after injection of Bupivacaine Hydrochloride Injection. (5.2)
- Methemoglobinemia: Cases of methemoglobinemia have been reported in association with local anesthetic use. See full prescribing information for more detail on managing these risks. (5.3)
- Chondrolysis with Intra-Articular Infusion: Intra-articular infusions of local anesthetics including Bupivacaine Hydrochloride Injection following arthroscopic and other surgical procedures is an unapproved use, and there have been post-marketing reports of chondrolysis in patients receiving such infusions. (5.5)
- Risk of Cardiac Arrest with Intravenous Regional Anesthesia Use (Bier Block): There have been reports of cardiac arrest and death during the use of bupivacaine for intravenous regional anesthesia (Bier Block). (5.7)
- Risk of Systemic Toxicities with Unintended Intravascular or Intrathecal Injection: Unintended intravascular or intrathecal injection may be associated with systemic toxicities, including CNS or cardiorespiratory depression and coma, progressing ultimately to respiratory arrest. Aspirate for blood or cerebrospinal fluid (where applicable) prior to each dose. (5.9)

6 ADVERSE REACTIONS

Most common adverse reactions are related to the central nervous system and the cardiovascular system. (6)

To report SUSPECTED ADVERSE REACTIONS, contact Pfizer Inc. at 1-800-438-1985 or FDA at 1-800-FDA-1088 or www.fda.gov/medwatch.

7 DRUG INTERACTIONS

- Local Anesthetics: The toxic effects of local anesthetics are additive. Monitor for neurologic and cardiovascular effects when additional local anesthetics are administered. (7.1)
- Drugs Associated with Methemoglobinemia: Patients are at increased risk of developing methemoglobinemia when concurrently exposed to nitrates, nitrites, local anesthetics, antineoplastic agents, antibiotics, antimalarials, anticonvulsants, and other drugs. (7.5)
- Potent Inhalation Anesthetics: Serious dose-related cardiac arrhythmias may occur if preparations containing a vasoconstrictor such as epinephrine are used in patients during or following the administration of potent inhalation anesthetics. (7.6)

8 USE IN SPECIFIC POPULATIONS

- Pediatric Use: Administration of Bupivacaine Hydrochloride Injection in pediatric patients younger than 12 years is not recommended. (8.4)
- Geriatric Use: Patients 65 years and over, particularly those with hypertension, may be at increased risk for developing hypotension while undergoing anesthesia with Bupivacaine Hydrochloride Injection. (8.5)
- Moderate to Severe Hepatic Impairment: Consider increased monitoring for bupivacaine systemic toxicity. (8.6)

FULL PRESCRIBING INFORMATION

WARNING: RISK OF CARDIAC ARREST WITH USE OF BUPIVACAINE HYDROCHLORIDE INJECTION IN OBSTETRICAL ANESTHESIA

There have been reports of cardiac arrest with difficult resuscitation or death during use of Bupivacaine Hydrochloride Injection for epidural anesthesia in obstetrical patients. In most cases, this has followed use of the 0.75% (7.5 mg/mL) concentration. Resuscitation has been difficult or impossible despite apparently adequate preparation and appropriate management. Cardiac arrest has occurred after convulsions resulting from systemic toxicity, presumably following unintentional intravascular injection. The 0.75% (7.5 mg/mL) concentration of Bupivacaine Hydrochloride Injection is not recommended for obstetrical anesthesia and should be reserved for surgical procedures where a high degree of muscle relaxation and prolonged effect are necessary [see Warnings and Precautions (5.1)].

1 INDICATIONS AND USAGE

Bupivacaine Hydrochloride Injection is indicated in adults for the production of local or regional anesthesia or analgesia for surgery, dental and oral surgery procedures, diagnostic and therapeutic procedures, and for obstetrical procedures. Specific concentrations and presentations of Bupivacaine Hydrochloride Injection are recommended for each type of block indicated to produce local or regional anesthesia or analgesia [see Dosage and Administration (2.2)].

Limitations of Use

Not all blocks are indicated for use with Bupivacaine Hydrochloride Injection given clinically significant risks associated with use [see Dosage and Administration (2.2), Contraindications (4), Warnings and Precautions (5.1, 5.5, 5.7, 5.9)] .

2 DOSAGE AND ADMINISTRATION

2.1 Important Dosage and Administration Information

- Bupivacaine Hydrochloride Injection is not for intrathecal use.
- Discard unused portions of solution not containing preservatives, i.e., those supplied in single-dose vials, following initial use.
- Visually inspect this product for particulate matter and discoloration prior to administration whenever solution and container permit. Bupivacaine Hydrochloride Injection are clear, colorless solutions. Do not administer solutions which are discolored or contain particulate matter.
- Mixing or the prior or intercurrent use of any other local anesthetic with Bupivacaine Hydrochloride Injection is not recommended because of insufficient data on the clinical use of such mixtures.

Administration Precautions

- Bupivacaine Hydrochloride Injection Injection are to be administered in carefully adjusted dosages by or under the supervision of experienced clinicians who are well versed in the diagnosis and management of dose-related toxicity and other acute emergencies which might arise from the block to be employed.
- Use Bupivacaine Hydrochloride Injection only if the following are immediately available: oxygen, cardiopulmonary resuscitative equipment and drugs, and the personnel resources needed for proper management of toxic reactions and related emergencies [see Warnings and Precautions (5.2), Adverse Reactions (6), Overdosage (10)] .
- The toxic effects of local anesthetics are additive. Monitor for neurologic and cardiovascular effects related to local anesthetic systemic toxicity when additional local anesthetics are administered with Bupivacaine Hydrochloride Injection [see Warnings and Precautions (5.2), Drug Interactions (7.1), Overdosage (10)] .
- Aspirate for blood or cerebrospinal fluid (where applicable) prior to injecting Bupivacaine Hydrochloride Injection, both the initial dose and all subsequent doses, to avoid intravascular or intrathecal injection. However, a negative aspiration for blood or cerebrospinal fluid does not ensure against an intravascular or intrathecal injection [see Warnings and Precautions (5.9)] .
- Avoid rapid injection of a large volume of Bupivacaine Hydrochloride Injection and use fractional (incremental) doses when feasible.
- During major regional nerve blocks, such as those of the brachial plexus or lower extremity, the patient should have an indwelling intravenous catheter to assure adequate intravenous access. The lowest dosage of Bupivacaine Hydrochloride Injection that results in effective anesthesia should be used to avoid high plasma levels and serious adverse reactions.
- Perform careful and constant monitoring of cardiovascular and respiratory (adequacy of oxygenation and ventilation) vital signs and the patient's level of consciousness after each local anesthetic injection.

2.2 Recommended Concentrations and Dosages of Bupivacaine Hydrochloride Injection

The dosage of Bupivacaine Hydrochloride Injection administered varies with the anesthetic procedure, the area to be anesthetized, the vascularity of the tissues, the number of neuronal segments to be blocked, the depth of anesthesia and degree of muscle relaxation required, the duration of anesthesia desired, individual tolerance, and the physical condition of the patient. Administer the smallest dosage and concentration required to produce the desired result.

The types of block and recommended Bupivacaine Hydrochloride Injection concentrations are shown in Table 1.

Table 1. Types of Block and Recommended Bupivacaine Hydrochloride Injection Concentrations

Type of Block | Bupivacaine Hydrochloride injection
Type of Block | 0.25% (2.5 mg/mL) | 0.5% (5 mg/mL) | 0.75% (7.5 mg/mL)*
Local infiltration | ✓
Peripheral nerve block | ✓ | ✓
Retrobulbar block |  |  | ✓
Sympathetic block | ✓
Caudal block | ✓ | ✓
Lumbar epidural block | ✓ | ✓ | ✓ (not for obstetrical anesthesia)
Epidural test dose
Dental block

* Bupivacaine Hydrochloride injection 0.75% (7.5 mg/mL) is not recommended for nonobstetrical surgical procedures in pregnant patients.

✓= indicated use [see Warnings and Precautions (5.1)].

At recommended dosages, Bupivacaine Hydrochloride produces complete sensory block, but the effect on motor function differs among the three concentrations. Table 2 provides information on the expected effect on motor function for the three concentrations.

Table 2. Types of Block and Recommended Bupivacaine Hydrochloride Injection Concentrations
Bupivacaine Hydrochloride Injection Concentration | Motor Function
0.25% (2.5 mg/mL) | When used for caudal, epidural, or peripheral nerve block, produces incomplete motor block. Should be used for operations in which muscle relaxation is not important, or when another means of providing muscle relaxation is used concurrently. Onset of action may be slower than with the 0.5% (5 mg/mL) or 0.75% (7.5 mg/mL) solutions.
0.5% (5 mg/mL) | Provides motor blockade for caudal, epidural, or nerve block, but muscle relaxation may be inadequate for operations in which complete muscle relaxation is essential.
0.75% (7.5 mg/mL) | Produces complete motor block. Most useful for epidural block in abdominal operations requiring complete muscle relaxation, and for retrobulbar anesthesia. Not for obstetrical anesthesia.

The duration of anesthesia with Bupivacaine Hydrochloride Injection is such that for most indications, a single dose is sufficient.

The maximum dosage limit within the recommended dosage range must be individualized in each case after evaluating the size and physical status of the patient, as well as the anticipated rate of systemic absorption from a particular injection site.

The dosages in Table 3 are recommended as a guide for use in the average adult. These doses may be repeated once every three hours. Do not exceed a total daily dosage of 400 mg in 24 hours. The duration of anesthetic effect may be prolonged by the addition of epinephrine.

Table 3. Recommended Concentrations and Doses of Bupivacaine Hydrochloride Injection in Adults
Type of Block | Concentration of Bupivacaine Hydrochloride Injection | Each Dose |  | Motor Block [With continuous (intermittent) techniques, repeat doses increase the degree of motor block. The first repeat dose of 0.5% (5 mg/mL) may produce complete motor block. Intercostal nerve block with 0.25% (2.5 mg/mL) also may produce complete motor block for intra-thoracic and upper intra-abdominal surgery.]
Type of Block | Concentration of Bupivacaine Hydrochloride Injection | mL | mg of Bupivacaine Hydrochloride Injection | Motor Block [With continuous (intermittent) techniques, repeat doses increase the degree of motor block. The first repeat dose of 0.5% (5 mg/mL) may produce complete motor block. Intercostal nerve block with 0.25% (2.5 mg/mL) also may produce complete motor block for intra-thoracic and upper intra-abdominal surgery.]
Local infiltration | 0.25% (2.5 mg/mL) [Solutions with or without epinephrine (i.e., applies to Bupivacaine Hydrochloride Injection.] | Up to 70 (without epinephrine) | Up to 175 (without epinephrine) | ―
Local infiltration | 0.25% (2.5 mg/mL) [Solutions with or without epinephrine (i.e., applies to Bupivacaine Hydrochloride Injection.] | Up to 90 (with epinephrine) | Up to 225 (with epinephrine) | ―
Peripheral nerve block | 0.5% (5 mg/mL) | 5–35 (without epinephrine) | 25–175 (without epinephrine) | moderate to complete
Peripheral nerve block | 0.5% (5 mg/mL) | 5–45 (with epinephrine) | 25–225 (with epinephrine) | moderate to complete
Peripheral nerve block | 0.25% (2.5 mg/mL) | 5–70 (without epinephrine) | 12.5–175 (without epinephrine) | moderate to complete
Peripheral nerve block | 0.25% (2.5 mg/mL) | 5–90 (with epinephrine) | 12.5–225 (with epinephrine) | moderate to complete
Retrobulbar block [see Dosage and Administration (2.6)] | 0.75% (7.5 mg/mL) | 2–4 | 15–30 | complete
Sympathetic block | 0.25% (2.5 mg/mL) | 20–50 | 50–125 | ―
Caudal block [see Dosage and Administration (2.4)] | 0.5% (5 mg/mL) | 15–30 | 75–150 | moderate to complete
Caudal block [see Dosage and Administration (2.4)] | 0.25% (2.5 mg/mL) | 15–30 | 37.5–75 | moderate
Lumbar epidural block [see Dosage and Administration (2.3)] | 0.75% (7.5 mg/mL) [For single-dose use; not for intermittent epidural technique. Not for obstetrical anesthesia.] | 10–20 | 75–150 | complete
Lumbar epidural block [see Dosage and Administration (2.3)] | 0.5% (5 mg/mL) | 10–20 | 50–100 | moderate to complete
Lumbar epidural block [see Dosage and Administration (2.3)] | 0.25% (2.5 mg/mL) | 10–20 | 25–50 | partial to moderate

2.3 Use in Epidural Anesthesia

During epidural administration, administer Bupivacaine Hydrochloride Injection, 0.5% (5 mg/mL) and 0.75% (7.5 mg/mL) solutions in incremental doses of 3 mL to 5 mL with sufficient time between doses to detect toxic manifestations of unintentional intravascular or intrathecal injection. Administer injections slowly, with frequent aspirations before and during the injection to avoid intravascular injection. Perform syringe aspirations before and during each supplemental injection in continuous (intermittent) catheter techniques. In obstetrics, use ONLY the 0.5% (5 mg/mL) and 0.25% (2.5 mg/mL) concentrations of Bupivacaine Hydrochloride Injection [see Warnings and Precautions (5.1)]; incremental doses of 3 mL to 5 mL of the 0.5% (5 mg/mL) solution not exceeding 50 mg to 100 mg at any dosing interval are recommended. Repeat doses should be preceded by a test dose containing epinephrine if not clinically contraindicated. Use only the single-dose vials for caudal or epidural anesthesia; avoid use of the multiple-dose vials for these procedures, which contain a preservative [see Dosage and Administration (2.1), Warnings and Precautions (5.9)] .

2.6 Use in Ophthalmic Surgery

When Bupivacaine Hydrochloride Injection 0.75% (7.5 mg/mL) is used for retrobulbar block, complete corneal anesthesia usually precedes onset of clinically acceptable external ocular muscle akinesia. Therefore, presence of akinesia rather than anesthesia alone should determine readiness of the patient for surgery [see Warnings and Precautions (5.15)] .

3 DOSAGE FORMS AND STRENGTHS

Bupivacaine Hydrochloride Injection, USP is a clear, colorless solution available as:

- 0.5% (50 mg/10 mL) (5 mg/mL) in single-dose teartop vials.

4 CONTRAINDICATIONS

Bupivacaine Hydrochloride Injection is contraindicated in:

- obstetrical paracervical block anesthesia. Its use in this technique has resulted in fetal bradycardia and death.
- intravenous regional anesthesia (Bier Block) [see Warnings and Precautions (5.7)].
- patients with a known hypersensitivity to bupivacaine or to any local anesthetic agent of the amide-type or to other components of Bupivacaine Hydrochloride Injection.

5 WARNINGS AND PRECAUTIONS

5.1 Risk of Cardiac Arrest with Use of Bupivacaine Hydrochloride Injection in Obstetrical Anesthesia

There have been reports of cardiac arrest with difficult resuscitation or death during use of Bupivacaine Hydrochloride Injection for epidural anesthesia in obstetrical patients. In most cases, this has followed use of the 0.75% (7.5 mg/mL) concentration. Resuscitation has been difficult or impossible despite apparently adequate preparation and appropriate management. Cardiac arrest has occurred after convulsions resulting from systemic toxicity, presumably following unintentional intravascular injection. The 0.75% (7.5 mg/mL) concentration of Bupivacaine Hydrochloride Injection is not recommended for obstetrical anesthesia and should be reserved for surgical procedures where a high degree of muscle relaxation and prolonged effect are necessary.

5.2 Dose-Related Toxicity

The safety and effectiveness of Bupivacaine Hydrochloride Injection depend on proper dosage, correct technique, adequate precautions, and readiness for emergencies. Careful and constant monitoring of cardiovascular and respiratory (adequacy of ventilation) vital signs and the patient's state of consciousness should be performed after injection of Bupivacaine Hydrochloride Injection solutions.

Possible early warning signs of central nervous system (CNS) toxicity are restlessness, anxiety, incoherent speech, lightheadedness, numbness and tingling of the mouth and lips, metallic taste, tinnitus, dizziness, blurred vision, tremors, twitching, CNS depression, or drowsiness. Delay in proper management of dose-related toxicity, underventilation from any cause, and/or altered sensitivity may lead to the development of acidosis, cardiac arrest, and, possibly, death.

During major regional nerve blocks, such as those of the brachial plexus or lower extremity, the patient should have an indwelling intravenous catheter to assure adequate intravenous access. Use the lowest dosage of Bupivacaine Hydrochloride Injection that results in effective anesthesia to avoid high plasma levels and serious adverse effects. Avoid rapid injection of a large volume of Bupivacaine Hydrochloride Injection solution and administer fractional (incremental) doses when feasible.

Injection of repeated doses of Bupivacaine Hydrochloride Injection may cause significant increases in plasma levels with each repeated dose due to slow accumulation of the drug or its metabolites, or to slow metabolic degradation. Tolerance to elevated blood levels varies with the status of the patient. Debilitated, elderly patients and acutely ill patients should be given reduced doses commensurate with their age and physical status.

5.3 Methemoglobinemia

Cases of methemoglobinemia have been reported in association with local anesthetic use. Although all patients are at risk for methemoglobinemia, patients with glucose-6-phosphate dehydrogenase deficiency, congenital or idiopathic methemoglobinemia, cardiac or pulmonary compromise, infants under 6 months of age, and concurrent exposure to oxidizing agents or their metabolites are more susceptible to developing clinical manifestations of the condition [see Drug Interactions (7.5)] . If local anesthetics must be used in these patients, close monitoring for symptoms and signs of methemoglobinemia is recommended.

Signs of methemoglobinemia may occur immediately or may be delayed some hours after exposure, and are characterized by a cyanotic skin discoloration and/or abnormal coloration of the blood. Methemoglobin levels may continue to rise; therefore, immediate treatment is required to avert more serious CNS and cardiovascular adverse effects, including seizures, coma, arrhythmias, and death. Discontinue Bupivacaine Hydrochloride Injection and any other oxidizing agents. Depending on the severity of the signs and symptoms, patients may respond to supportive care, i.e., oxygen therapy, hydration. A more severe clinical presentation may require treatment with methylene blue, exchange transfusion, or hyperbaric oxygen.

5.5 Chondrolysis with Intra-Articular Infusion

Intra-articular infusions of local anesthetics including Bupivacaine Hydrochloride Injection following arthroscopic and other surgical procedures is an unapproved use, and there have been post-marketing reports of chondrolysis in patients receiving such infusions. The majority of reported cases of chondrolysis have involved the shoulder joint; cases of gleno-humeral chondrolysis have been described in pediatric and adult patients following intra-articular infusions of local anesthetics with and without epinephrine for periods of 48 to 72 hours. There is insufficient information to determine whether shorter infusion periods are associated with chondrolysis. The time of onset of symptoms, such as joint pain, stiffness and loss of motion can be variable, but may begin as early as the 2ndmonth after surgery. Currently, there is no effective treatment for chondrolysis; patients who experienced chondrolysis have required additional diagnostic and therapeutic procedures and some required arthroplasty or shoulder replacement.

5.7 Risk of Cardiac Arrest with Intravenous Regional Anesthesia Use (Bier Block)

There have been reports of cardiac arrest and death during the use of bupivacaine for intravenous regional anesthesia (Bier Block). Information on safe dosages and techniques of administration of Bupivacaine Hydrochloride Injection in this procedure is lacking. Therefore, Bupivacaine Hydrochloride Injection is contraindicated for use with this technique [see Contraindications (4)] .

5.9 Risk of Systemic Toxicities with Unintended Intravascular or Intrathecal Injection

Unintended intravascular or intrathecal injection of Bupivacaine Hydrochloride Injection may be associated with systemic toxicities, including CNS or cardiorespiratory depression and coma, progressing ultimately to respiratory arrest. Unintentional intrathecal injection during the intended performance of caudal or lumbar epidural block or nerve blocks near the vertebral column has resulted in underventilation or apnea ("Total or High Spinal"). A high spinal has been characterized by paralysis of the legs, loss of consciousness, respiratory paralysis, and bradycardia [see Adverse Reactions (6)] .

Aspirate for blood or cerebrospinal fluid (where applicable) before injecting Bupivacaine Hydrochloride Injection, both the initial dose and all subsequent doses, to avoid intravascular or intrathecal injection. However, a negative aspiration for blood or cerebrospinal fluid does not ensure against an intravascular or intrathecal injection.

5.10 Risk of Toxicity in Patients with Hepatic Impairment

Because amide local anesthetics such as bupivacaine are metabolized by the liver, consider reduced dosing and increased monitoring for bupivacaine systemic toxicity in patients with moderate to severe hepatic impairment who are treated with Bupivacaine Hydrochloride Injection, especially with repeat doses [see Use in Specific Populations (8.6)].

5.11 Risk of Use in Patients with Impaired Cardiovascular Function

Bupivacaine Hydrochloride Injection should be given in reduced doses in patients with impaired cardiovascular function (e.g., hypotension, heartblock) because they may be less able to compensate for functional changes associated with the prolongation of AV conduction produced by Bupivacaine Hydrochloride Injection. Monitor patients closely for blood pressure, heart rate, and ECG changes.

5.14 Risk of Adverse Reactions with Use in Head and Neck Area

Small doses of local anesthetics (e.g., Bupivacaine Hydrochloride Injection) injected into the head and neck area, including retrobulbar, dental, and stellate ganglion blocks, may produce adverse reactions similar to systemic toxicity seen with unintentional intravascular injections of larger doses. The injection procedures require the utmost care. Confusion, convulsions, respiratory depression, and/or respiratory arrest, and cardiovascular stimulation or depression have been reported. These reactions may be due to intra-arterial injection of the local anesthetic with retrograde flow to the cerebral circulation. They may also be due to puncture of the dural sheath of the optic nerve during retrobulbar block with diffusion of any local anesthetic along the subdural space to the midbrain. Monitor circulation and respiration and constantly observe patients receiving Bupivacaine Hydrochloride Injection blocks. Resuscitative equipment and drugs, and personnel for treating adverse reactions should be immediately available. Dosage recommendations should not be exceeded [see Dosage and Administration (2.2)].

5.15 Risk of Respiratory Arrest with Use in Ophthalmic Surgery

Clinicians who perform retrobulbar blocks should be aware that there have been reports of respiratory arrest following local anesthetic injection. Prior to retrobulbar block (e.g., with Bupivacaine Hydrochloride Injection), as with all other regional procedures, resuscitative equipment and drugs, and personnel to manage respiratory arrest or depression, convulsions, and cardiac stimulation or depression should be immediately available [see Warnings and Precautions (5.14)]. As with other anesthetic procedures, patients should be constantly monitored following ophthalmic blocks for signs of these adverse reactions, which may occur following relatively low total doses.

A concentration of 0.75% bupivacaine is indicated for retrobulbar block; however, this concentration is not indicated for any other peripheral nerve block, including the facial nerve, and not indicated for local infiltration, including the conjunctiva [see Indications and Usage (1)].

5.16 Risk of Inadvertent Trauma to Tongue, Lips, and Buccal Mucosa in Dental Applications

Because of the long duration of anesthesia, when Bupivacaine Hydrochloride injection with epinephrine [0.5% (5 mg/mL) of bupivacaine] is used for dental injections, warn patients about the possibility of inadvertent trauma to tongue, lips, and buccal mucosa and advise them not to chew solid foods until sensation returns [see Patient Counseling Information (17)] .

6 ADVERSE REACTIONS

The following clinically significant adverse reactions have been reported and described in the Warnings and Precautions section of the labeling:

- Cardiac Arrest in Obstetrical Anesthesia [see Warnings and Precautions (5.1)]
- Dose-Related Toxicity [see Warnings and Precautions (5.2)]
- Methemoglobinemia [see Warnings and Precautions (5.3)]
- Chondrolysis with Intra-Articular Infusion [see Warnings and Precautions (5.5)]
- Cardiac Arrest with Intravenous Regional Anesthesia Use [see Contraindications (4), Warnings and Precautions (5.7)]
- Systemic Toxicities with Unintended Intravascular or Intrathecal Injection [see Warnings and Precautions (5.9)]
- Respiratory Arrest Following Retrobulbar Block [see Warnings and Precautions (5.15)]

The following adverse reactions from voluntary reports or clinical studies have been reported with bupivacaine. Because many of these reactions were reported voluntarily from a population of uncertain size, it is not always possible to reliably estimate their frequency or establish a causal relationship to drug exposure.

Adverse reactions to Bupivacaine Hydrochloride Injection are characteristic of those associated with other amide-type local anesthetics. A major cause of adverse reactions to this group of drugs is excessive plasma levels, which may be due to overdosage, unintentional intravascular injection, or slow metabolic degradation.

The most commonly encountered acute adverse reactions that demand immediate counter-measures were related to the CNS and the cardiovascular system. These adverse reactions were generally dose-related and due to high plasma levels which may have resulted from overdosage, rapid absorption from the injection site, diminished tolerance, or from unintentional intravascular injection of the local anesthetic solution. In addition to systemic dose-related toxicity, unintentional intrathecal injection of drug during the intended performance of caudal or lumbar epidural block or nerve blocks near the vertebral column (especially in the head and neck region) has resulted in underventilation or apnea ("Total or High Spinal"). Also, hypotension due to loss of sympathetic tone and respiratory paralysis or underventilation due to cephalad extension of the motor level of anesthesia have occurred. This has led to secondary cardiac arrest when untreated.

Nervous System Disorders

Adverse reactions were characterized by excitation and/or depression of the central nervous system and included restlessness, anxiety, dizziness, tinnitus, blurred vision, tremors, convulsions, drowsiness, unconsciousness, respiratory arrest, nausea, vomiting, chills, pupillary constriction.

In the practice of caudal or lumbar epidural block, unintentional penetration of the subarachnoid space by the catheter or needle has occurred. Subsequent adverse effects may have depended partially on the amount of drug administered intrathecally and the physiological and physical effects of a dural puncture. A high spinal has been characterized by paralysis of the legs, loss of consciousness, respiratory paralysis, and bradycardia.

Neurologic effects following epidural or caudal anesthesia have included spinal block of varying magnitude (including high or total spinal block); hypotension secondary to spinal block; urinary retention; fecal and urinary incontinence; loss of perineal sensation and sexual function; persistent anesthesia, paresthesia, weakness, paralysis of the lower extremities and loss of sphincter control, all of which had slow, incomplete, or no recovery; headache; backache; septic meningitis; meningismus; slowing of labor; increased incidence of forceps delivery; and cranial nerve palsies due to traction on nerves from loss of cerebrospinal fluid.

Neurologic effects following other procedures or routes of administration have included persistent anesthesia, paresthesia, weakness, paralysis, all with slow, incomplete, or no recovery.

Convulsions: Incidence varied with the procedure used and the total dose administered. In a survey of studies of epidural anesthesia, overt toxicity progressing to convulsions occurred in approximately 0.1% of local anesthetic administrations. The incidences of adverse neurologic reactions associated with the use of local anesthetics may be related to the total dose of local anesthetic administered and are also dependent upon the particular drug used, the route of administration, and the physical status of the patient.

Cardiac Disorders

High doses or unintentional intravascular injection have led to high plasma levels and related depression of the myocardium, decreased cardiac output, heartblock, hypotension, bradycardia, ventricular arrhythmias, including ventricular tachycardia and ventricular fibrillation, and cardiac arrest [see Warnings and Precautions (5.9)].

Immune System Disorders

Allergic-type reactions have occurred as a result of sensitivity to bupivacaine or to other formulation ingredients, such as the antimicrobial preservative methylparaben contained in multiple-dose vials or sulfites in epinephrine-containing solutions. These reactions were characterized by signs such as urticaria, pruritus, erythema, angioneurotic edema (including laryngeal edema), tachycardia, sneezing, nausea, vomiting, dizziness, syncope, excessive sweating, elevated temperature, and severe hypotension. Cross sensitivity among members of the amide-type local anesthetic group has been reported [see Warnings and Precautions (5.8)] .

7 DRUG INTERACTIONS

7.1 Local Anesthetics

The toxic effects of local anesthetics are additive. If coadministration of other local anesthetics with Bupivacaine Hydrochloride Injection cannot be avoided, monitor patients for neurologic and cardiovascular effects related to local anesthetic systemic toxicity [see Dosage and Administration (2.1), Warnings and Precautions (5.2)] .

7.5 Drugs Associated with Methemoglobinemia

Patients who are administered Bupivacaine Hydrochloride Injection are at increased risk of developing methemoglobinemia when concurrently exposed to the following drugs, which could include other local anesthetics [see Warnings and Precautions (5.3)] .

Examples of Drugs Associated with Methemoglobinemia:
Class | Examples
Nitrates/Nitrites | nitric oxide, nitroglycerin, nitroprusside, nitrous oxide
Local anesthetics | articaine, benzocaine, bupivacaine, lidocaine, mepivacaine, prilocaine, procaine, ropivacaine, tetracaine
Antineoplastic agents | cyclophosphamide, flutamide, hydroxyurea, ifosfamide, rasburicase
Antibiotics | dapsone, nitrofurantoin, para-aminosalicylic acid, sulfonamides
Antimalarials | chloroquine, primaquine
Anticonvulsants | phenobarbital, phenytoin, sodium valproate
Other drugs | acetaminophen, metoclopramide, quinine, sulfasalazine

7.6 Potent Inhalation Anesthetics

Serious dose-related cardiac arrhythmias may occur if preparations containing a vasoconstrictor such as epinephrine are used in patients during or following the administration of potent inhalation anesthetics.

8 USE IN SPECIFIC POPULATIONS

8.1 Pregnancy

Risk Summary

Bupivacaine Hydrochloride Injection is contraindicated for obstetrical paracervical block anesthesia. Its use in this technique has resulted in fetal bradycardia and death [see Contraindications (4), Warnings and Precautions (5.1)].

There are no available data on use of Bupivacaine Hydrochloride Injection in pregnant women to inform a drug-associated risk of adverse developmental outcomes.

In animal studies, embryo-fetal lethality was noted when bupivacaine was administered subcutaneously to pregnant rabbits during organogenesis at clinically relevant doses. Decreased pup survival was observed in a rat pre- and post-natal developmental study (dosing from implantation through weaning) at a dose level comparable to the daily maximum recommended human dose (MRHD) on a body surface area (BSA) basis. Based on animal data, advise pregnant women of the potential risks to a fetus (see Data).

Local anesthetics rapidly cross the placenta, and when used for epidural, caudal, or pudendal block anesthesia, can cause varying degrees of maternal, fetal, and neonatal toxicity [see Clinical Pharmacology (12.3)]. The incidence and degree of toxicity depend upon the procedure performed, the type, and amount of drug used, and the technique of drug administration. Adverse reactions in the parturient, fetus, and neonate involve alterations of the CNS, peripheral vascular tone, and cardiac function.

If this drug is used during pregnancy, or if the patient becomes pregnant while taking this drug, inform the patient of the potential hazard to the fetus. The estimated background risk of major birth defects and miscarriage for the indicated populations are unknown. In the U.S. general population, the estimated background risk of major birth defects and miscarriage in clinically recognized pregnancies is 2–4% and 15–20%, respectively.

Clinical Considerations

Maternal Adverse Reactions

Maternal hypotension has resulted from regional anesthesia. Local anesthetics produce vasodilation by blocking sympathetic nerves. The supine position is dangerous in pregnant women at term because of aortocaval compression by the gravid uterus. Therefore, during treatment of systemic toxicity, maternal hypotension or fetal bradycardia following regional block, the parturient should be maintained in the left lateral decubitus position if possible, or manual displacement of the uterus off the great vessels be accomplished. Elevating the patient's legs will also help prevent decreases in blood pressure. The fetal heart rate also should be monitored continuously and electronic fetal monitoring is highly advisable.

Labor or Delivery

Epidural, caudal, or pudendal anesthesia may alter the forces of parturition through changes in uterine contractility or maternal expulsive efforts. Epidural anesthesia has been reported to prolong the second stage of labor by removing the parturient's reflex urge to bear down or by interfering with motor function. The use of obstetrical anesthesia may increase the need for forceps assistance.

The use of some local anesthetic drug products during labor and delivery may be followed by diminished muscle strength and tone for the first day or two of life. This has not been reported with bupivacaine.

It is extremely important to avoid aortocaval compression by the gravid uterus during administration of regional block to parturients. To do this, the patient must be maintained in the left lateral decubitus position or a blanket roll or sandbag may be placed beneath the right hip and gravid uterus displaced to the left.

Data

Animal Data

Bupivacaine hydrochloride produced developmental toxicity when administered subcutaneously to pregnant rats and rabbits at clinically relevant doses.

Bupivacaine hydrochloride was administered subcutaneously to rats at doses of 4.4, 13.3, & 40 mg/kg and to rabbits at doses of 1.3, 5.8, & 22.2 mg/kg during the period of organogenesis (implantation to closure of the hard palate). The high doses are comparable to the daily MRHD of 400 mg/day on a mg/m^2BSA basis. No embryo-fetal effects were observed in rats at the high dose which caused increased maternal lethality. An increase in embryo-fetal deaths was observed in rabbits at the high dose in the absence of maternal toxicity with the fetal No Observed Adverse Effect Level representing approximately 0.3 times the MRHD on a BSA basis.

In a rat pre- and post-natal developmental study (dosing from implantation through weaning) conducted at subcutaneous doses of 4.4, 13.3, & 40 mg/kg, decreased pup survival was observed at the high dose. The high dose is comparable to the daily MRHD of 400 mg/day on a BSA basis.

8.2 Lactation

Risk Summary

Lactation studies have not been conducted with bupivacaine. Bupivacaine has been reported to be excreted in human milk suggesting that the nursing infant could be theoretically exposed to a dose of the drug. Bupivacaine Hydrochloride Injection should be administered to lactating women only if clearly indicated. Studies assessing the effects of Bupivacaine Hydrochloride Injection in breastfed children have not been performed. Studies to assess the effect of Bupivacaine Hydrochloride Injection on milk production or excretion have not been performed. The developmental and health benefits of breastfeeding should be considered along with the mother's clinical need for bupivacaine and any potential adverse effects on the breastfed child from bupivacaine or from the underlying maternal condition.

8.4 Pediatric Use

Bupivacaine Hydrochloride Injection is approved for use in adults. Administration of Bupivacaine Hydrochloride Injection in pediatric patients younger than 12 years is not recommended.

Continuous infusions of bupivacaine in pediatric patients have been reported to result in high systemic levels of bupivacaine and seizures; high plasma levels may also be associated with cardiovascular abnormalities.

8.5 Geriatric Use

Patients 65 years and over, particularly those with hypertension, may be at increased risk for developing hypotension while undergoing anesthesia with Bupivacaine Hydrochloride Injection.

In clinical studies of bupivacaine, elderly patients reached the maximal spread of analgesia and maximal motor blockade more rapidly than younger adult patients.

Differences in various pharmacokinetic parameters have been observed between elderly and younger adult patients [see Clinical Pharmacology (12.3)].

This product is known to be substantially excreted by the kidney, and the risk of adverse reactions to this drug may be greater in patients with impaired renal function. Because elderly patients are more likely to have decreased renal function, care should be taken in dose selection, and it may be useful to monitor renal function. Elderly patients may require lower doses of Bupivacaine Hydrochloride Injection.

8.6 Hepatic Impairment

Amide-type local anesthetics, such as bupivacaine, are metabolized by the liver. Patients with severe hepatic impairment, because of their inability to metabolize local anesthetics normally, are at a greater risk of developing toxic plasma concentrations, and potentially local anesthetic systemic toxicity. Therefore, consider reduced dosing and increased monitoring for local anesthetic systemic toxicity in patients with moderate to severe hepatic impairment treated with Bupivacaine Hydrochloride Injection, especially with repeat doses [see Warnings and Precautions (5.10)] .

8.7 Renal Impairment

Bupivacaine is known to be substantially excreted by the kidney, and the risk of adverse reactions to this drug may be greater in patients with renal impairment. This should be considered when selecting the Bupivacaine Hydrochloride Injection dosage [see Use in Specific Populations (8.5)] .

10 OVERDOSAGE

Clinical Presentation

Acute emergencies from use of Bupivacaine Hydrochloride Injection are generally related to high plasma levels encountered during therapeutic use or to unintended intrathecal injection [see Warnings and Precautions (5.2, 5.9), Adverse Reactions (6)].

If not treated immediately, convulsions with simultaneous hypoxia, hypercarbia, and acidosis plus myocardial depression from the direct effects of bupivacaine may result in cardiac arrhythmias, bradycardia, asystole, ventricular fibrillation, or cardiac arrest. Respiratory abnormalities, including apnea, may occur. Hypoventilation or apnea due to unintentional intrathecal injection of Bupivacaine Hydrochloride Injection may produce these same signs and also lead to cardiac arrest if ventilatory support is not instituted. If cardiac arrest should occur, successful outcome may require prolonged resuscitative efforts.

Management

The first step in the management of systemic toxic reactions, as well as hypoventilation or apnea due to unintentional intrathecal injection of Bupivacaine Hydrochloride Injection, consists of immediateattention to the establishment and maintenance of a patent airway and effective assisted or controlled ventilation with 100% oxygen with a delivery system capable of permitting immediate positive airway pressure by mask. Endotracheal intubation, using drugs and techniques familiar to the clinician, may be indicated after initial administration of oxygen by mask if difficulty is encountered in the maintenance of a patent airway, or if prolonged ventilatory support (assisted or controlled) is indicated.

If necessary, use drugs to manage the convulsions. A bolus intravenous dose of a benzodiazepine will counteract CNS stimulation related to Bupivacaine Hydrochloride Injection. Immediately after the institution of ventilatory measures, evaluate the adequacy of the circulation. Supportive treatment of circulatory depression may require Advanced Cardiac Life Support measures.

11 DESCRIPTION

Bupivacaine Hydrochloride Injection contains bupivacaine hydrochloride, an amide local anesthetic, as the active pharmaceutical ingredient. The route of administration for Bupivacaine Hydrochloride Injection is by injection, for infiltration, perineural, caudal, epidural, or retrobulbar use. [see Warnings and Precautions (5.4)] .

Bupivacaine hydrochloride is 2-piperidinecarboxamide, 1-butyl- N-(2,6-dimethylphenyl)-, monohydrochloride, monohydrate. It is a white crystalline powder that is freely soluble in 95 percent ethanol, soluble in water, and slightly soluble in chloroform or acetone. It has the following structural formula:

Bupivacaine Hydrochloride Injection, USP is a clear and colorless sterile isotonic solution. Each mL of single-dose vial contains 5 mg of bupivacaine hydrochloride (equivalent to 4.44 mg of bupivacaine, respectively), sodium chloride for isotonicity, sodium hydroxide or hydrochloric acid to adjust the pH between 4 and 6.5, in water for injection.

12 CLINICAL PHARMACOLOGY

12.1 Mechanism of Action

Bupivacaine blocks the generation and the conduction of nerve impulses, presumably by increasing the threshold for electrical excitation in the nerve, by slowing the propagation of the nerve impulse, and by reducing the rate of rise of the action potential. In general, the progression of anesthesia is related to the diameter, myelination, and conduction velocity of affected nerve fibers. Clinically, the order of loss of nerve function is as follows: (1) pain, (2) temperature, (3) touch, (4) proprioception, and (5) skeletal muscle tone.

12.2 Pharmacodynamics

Systemic absorption of bupivacaine produces effects on the cardiovascular system and CNS. At blood concentrations achieved with normal therapeutic doses, changes in cardiac conduction, excitability, refractoriness, contractility, and peripheral vascular resistance are minimal. However, toxic blood concentrations depress cardiac conduction and excitability, which may lead to atrioventricular block, ventricular arrhythmias, and cardiac arrest, sometimes resulting in fatalities. In addition, myocardial contractility is depressed and peripheral vasodilation occurs, leading to decreased cardiac output and arterial blood pressure. These cardiovascular changes are more likely to occur after unintended intravascular injection of bupivacaine [see Warnings and Precautions (5.9)] .

Following systemic absorption, bupivacaine can produce CNS stimulation, CNS depression, or both. Apparent central stimulation is manifested as restlessness, tremors, and shivering, progressing to convulsions, followed by CNS depression and coma progressing ultimately to respiratory arrest. However, bupivacaine has a primary depressant effect on the medulla and on higher centers. The depressed stage may occur without a prior excited state.

The duration of local anesthesia after administration of Bupivacaine Hydrochloride Injection is longer than that observed after administration of other commonly used short-acting local anesthetics. There appears to be a period of analgesia that persists after the resolution of the block and return of sensation.

The onset of action following dental injections is usually 2 to 10 minutes and may last up to 7 hours.

12.3 Pharmacokinetics

Systemic plasma levels of bupivacaine following administration of Bupivacaine Hydrochloride Injection do not correlate with local efficacy.

Absorption

The rate of systemic absorption of bupivacaine is dependent upon the total dose and concentration of drug administered, the route of administration, the vascularity of the administration site, and the presence or absence of epinephrine in the anesthetic solution. A dilute concentration of epinephrine (1:200,000) usually reduces the rate of absorption and peak plasma concentration of bupivacaine, permitting the use of moderately larger total doses and sometimes prolonging the duration of action [see Dosage and Administration (2)] .

After injection of Bupivacaine Hydrochloride Injection for caudal, epidural, or peripheral nerve block, peak levels of bupivacaine in the blood are reached in 30 to 45 minutes, followed by a decline to insignificant levels during the next three to six hours.

Distribution

Bupivacaine appears to cross the placenta by passive diffusion. The rate and degree of diffusion is governed by (1) the degree of plasma protein binding, (2) the degree of ionization, and (3) the degree of lipid solubility. Fetal/maternal ratios of bupivacaine appear to be inversely related to the degree of plasma protein binding, because only the free, unbound drug is available for placental transfer. Bupivacaine with a high protein binding capacity (95%) has a low fetal/maternal ratio (0.2 to 0.4). The extent of placental transfer is also determined by the degree of ionization and lipid solubility of the drug. Lipid soluble, nonionized drugs readily enter the fetal blood from the maternal circulation.

Depending upon the route of administration, bupivacaine is distributed to some extent to all body tissues, with high concentrations found in highly perfused organs such as the liver, lungs, heart, and brain.

Pharmacokinetic studies on the plasma profile of bupivacaine after direct intravenous injection (Bupivacaine Hydrochloride Injection is not approved for intravenous use) suggest a three-compartment open model. The first compartment is represented by the rapid intravascular distribution of the drug. The second compartment represents the equilibration of the drug throughout the highly perfused organs such as the brain, myocardium, lungs, kidneys, and liver. The third compartment represents an equilibration of the drug with poorly perfused tissues, such as muscle and fat.

Elimination

The half-life of bupivacaine in adults is 2.7 hours.

Metabolism

Amide-type local anesthetics such as bupivacaine are metabolized primarily in the liver via conjugation with glucuronic acid. Pipecoloxylidine is the major metabolite of bupivacaine. The elimination of drug from tissue distribution depends largely upon the availability of binding sites in the circulation to carry it to the liver where it is metabolized.

Excretion

The kidney is the main excretory organ for most local anesthetics and their metabolites. Urinary excretion is affected by urinary perfusion and factors affecting urinary pH. Only 6% of bupivacaine is excreted unchanged in the urine.

Specific Populations

Geriatric Patients

Elderly patients exhibited higher peak plasma concentrations than younger patients following administration of Bupivacaine Hydrochloride Injection. The total plasma clearance was decreased in these patients [see Use in Specific Populations (8.5)] .

Patients with Hepatic Impairment

Various pharmacokinetic parameters of the local anesthetics can be significantly altered by the presence of hepatic disease. Patients with hepatic disease, especially those with severe hepatic disease, may be more susceptible to the potential toxicities of the amide-type local anesthetics [see Use in Specific Populations (8.6)] .

Patients with Renal Impairment

Various pharmacokinetic parameters of the local anesthetics can be significantly altered by the presence of renal disease, factors affecting urinary pH, and renal blood flow [see Use in Specific Populations (8.5, 8.7)] .

13 NONCLINICAL TOXICOLOGY

13.1 Carcinogenesis, Mutagenesis, Impairment of Fertility

Carcinogenesis

Long-term studies in animals to evaluate the carcinogenic potential of bupivacaine hydrochloride have not been conducted.

Mutagenesis

The mutagenic potential of bupivacaine hydrochloride has not been determined.

Impairment of Fertility

The effect of bupivacaine on fertility has not been determined.

16 HOW SUPPLIED/STORAGE AND HANDLING

STORAGE AND HANDLING

Store at 20 °C to 25 °C (68 °F to 77 °F); excursions permitted between 15 °C to 30 °C (59 °F to 86 °F). [See USP Controlled Room Temperature.]

Bupivacaine Hydrochloride Injection, USP─ Solutions of bupivacaine hydrochloride may be autoclaved. Autoclave at 15-pound pressure, 121 °C (250 °F) for 15 minutes. This product is clear and colorless. Do not use the solution if it is discolored or if it contains a precipitate.

Unit of Sale | Concentration
NDC 0409-1162-01 Tray of 25 single-dose teartop vials | 0.5% 50 mg/10 mL (5 mg/mL)
NDC 0409-1162-02 Tray of 25 single-dose teartop vials | 0.5% 150 mg/30 mL (5 mg/mL)

For single-dose vials: Discard unused portion.

17 PATIENT COUNSELING INFORMATION

Allergic-Type Reactions

Assess if the patient has had allergic-type reactions to amide-type local anesthetics [see Contraindications (4), Adverse Reactions (6)].

Temporary Loss of Sensation and Motor Activity After Caudal or Epidural Anesthesia

When appropriate, patients should be informed in advance that they may experience temporary loss of sensation and motor activity, usually in the lower half of the body, following proper administration of caudal or epidural anesthesia.

Instructions After Dental Injection of Bupivacaine Hydrochloride Injection

Advise patients receiving dental injections of Bupivacaine Hydrochloride Injection not to chew solid foods or to test the anesthetized area by biting or probing until anesthesia has worn off (up to 7 hours) [see Warnings and Precautions (5.16)].

Methemoglobinemia

Inform patients that use of local anesthetics may cause methemoglobinemia, a serious condition that must be treated promptly. Advise patients or caregivers to seek immediate medical attention if they or someone in their care experience the following signs or symptoms: pale, gray, or blue colored skin (cyanosis); headache; rapid heart rate; shortness of breath; lightheadedness; or fatigue [see Warnings and Precautions (5.3)].

This product's labeling may have been updated. For the most recent prescribing information, please visit www.pfizer.com.

Distributed by Hospira, Inc., Lake Forest, IL 60045 USA

LAB-1176-6.0

Triamcinolone Acetonide Injectable Suspension, USP

NOT FOR USE IN NEONATES
CONTAINS BENZYL ALCOHOL

For Intramuscular or Intra-articular Use Only

NOT FOR INTRAVENOUS, INTRADERMAL, INTRAOCULAR, EPIDURAL, OR INTRATHECAL USE

DESCRIPTION

Triamcinolone acetonide injectable suspension, USP is a synthetic glucocorticoid corticosteroid with anti-inflammatory action. THIS FORMULATION IS SUITABLE FOR INTRAMUSCULAR AND INTRA-ARTICULAR USE ONLY. THIS FORMULATION IS NOT FOR INTRADERMAL INJECTION.

Each mL of the sterile aqueous suspension provides 40 mg triamcinolone acetonide, USP, with 0.65% sodium chloride for isotonicity, 0.99% (w/v) benzyl alcohol as a preservative, 0.75% carboxymethylcellulose sodium, and 0.04% polysorbate 80 in an aqueous suspension. Sodium hydroxide or hydrochloric acid may be present to adjust pH to 5.0 to 7.5. At the time of manufacture, the air in the container is replaced by nitrogen.

The chemical name for triamcinolone acetonide is 9-Fluoro-11β,16α,17,21-tetrahydroxypregna-1,4-diene-3,20-dione cyclic 16,17-acetal with acetone. Its structural formula is:

MW 434.50

Triamcinolone acetonide, USP occurs as a white to cream-colored, crystalline powder having not more than a slight odor and is practically insoluble in water and very soluble in alcohol.

CLINICAL PHARMACOLOGY

Glucocorticoids, naturally occurring and synthetic, are adrenocortical steroids that are readily absorbed from the gastrointestinal tract.

Naturally occurring glucocorticoids (hydrocortisone and cortisone), which also have salt-retaining properties, are used as replacement therapy in adrenocortical deficiency states. Synthetic analogs such as triamcinolone are primarily used for their anti-inflammatory effects in disorders of many organ systems.

Triamcinolone acetonide injectable suspension has an extended duration of effect which may be sustained over a period of several weeks. Studies indicate that following a single intramuscular dose of 60 mg to 100 mg of triamcinolone acetonide, adrenal suppression occurs within 24 to 48 hours and then gradually returns to normal, usually in 30 to 40 days. This finding correlates closely with the extended duration of therapeutic action achieved with the drug.

INDICATIONS AND USAGE

Intramuscular

Where oral therapy is not feasible, injectable corticosteroid therapy, including triamcinolone acetonide injectable suspension is indicated for intramuscularuseas follows:

Allergic states:Control of severe or incapacitating allergic conditions intractable to adequate trials of conventional treatment in asthma, atopic dermatitis, contact dermatitis, drug hypersensitivity reactions, perennial or seasonal allergic rhinitis, serum sickness, transfusion reactions.

Dermatologic diseases:Bullous dermatitis herpetiformis, exfoliative erythroderma, mycosis fungoides, pemphigus, severe erythema multiforme (Stevens-Johnson syndrome).

Endocrine disorders:Primary or secondary adrenocortical insufficiency (hydrocortisone or cortisone is the drug of choice; synthetic analogs may be used in conjunction with mineralocorticoids where applicable; in infancy, mineralocorticoid supplementation is of particular importance), congenital adrenal hyperplasia, hypercalcemia associated with cancer, nonsuppurative thyroiditis.

Gastrointestinal diseases:To tide the patient over a critical period of the disease in regional enteritis and ulcerative colitis.

Hematologic disorders:Acquired (autoimmune) hemolytic anemia, Diamond-Blackfan anemia, pure red cell aplasia, selected cases of secondary thrombocytopenia.

Miscellaneous:Trichinosis with neurologic or myocardial involvement, tuberculous meningitis with subarachnoid block or impending block when used with appropriate antituberculous chemotherapy.

Neoplastic diseases:For the palliative management of leukemias and lymphomas.

Nervous system:Acute exacerbations of multiple sclerosis; cerebral edema associated with primary or metastatic brain tumor or craniotomy.

Ophthalmic diseases:Sympathetic ophthalmia, temporal arteritis, uveitis and ocular inflammatory conditions unresponsive to topical corticosteroids.

Renal diseases:To induce diuresis or remission of proteinuria in idiopathic nephrotic syndrome or that due to lupus erythematosus.

Respiratory diseases:Berylliosis, fulminating or disseminated pulmonary tuberculosis when used concurrently with appropriate antituberculous chemotherapy, idiopathic eosinophilic pneumonias, symptomatic sarcoidosis.

Rheumatic disorders:As adjunctive therapy for short-term administration (to tide the patient over an acute episode or exacerbation) in acute gouty arthritis; acute rheumatic carditis; ankylosing spondylitis; psoriatic arthritis; rheumatoid arthritis, including juvenile rheumatoid arthritis (selected cases may require low-dose maintenance therapy). For the treatment of dermatomyositis, polymyositis and systemic lupus erythematosus.

Intra-Articular

The intra-articular or soft tissue administrationof triamcinolone acetonide injectable suspension is indicated as adjunctive therapy for short-term administration (to tide the patient over an acute episode or exacerbation) in acute gouty arthritis, acute and subacute bursitis, acute nonspecific tenosynovitis, epicondylitis, rheumatoid arthritis, synovitis of osteoarthritis.

CONTRAINDICATIONS

Triamcinolone acetonide injectable suspension is contraindicated in patients who are hypersensitive to any components of this product (see WARNINGS: General).

Intramuscular corticosteroid preparations are contraindicated for idiopathic thrombocytopenic purpura.

WARNINGS

Serious Neurologic Adverse Reactions with Epidural Administration

Serious neurologic events, some resulting in death, have been reported with epidural injection of corticosteroids (see WARNINGS: Neurologic). Specific events reported include, but are not limited to, spinal cord infarction, paraplegia, quadriplegia, cortical blindness, and stroke. These serious neurologic events have been reported with and without use of fluoroscopy. The safety and effectiveness of epidural administration of corticosteroids have not been established, and corticosteroids are not approved for this use.

General

Exposure to excessive amounts of benzyl alcohol has been associated with toxicity (hypotension, metabolic acidosis), particularly in neonates, and an increased incidence of kernicterus, particularly in small preterm infants. There have been rare reports of deaths, primarily in preterm infants, associated with exposure to excessive amounts of benzyl alcohol. The amount of benzyl alcohol from medications is usually considered negligible compared to that received in flush solutions containing benzyl alcohol. Administration of high dosages of medications containing this preservative must take into account the total amount of benzyl alcohol administered. The amount of benzyl alcohol at which toxicity may occur is not known. If the patient requires more than the recommended dosages or other medications containing this preservative, the practitioner must consider the daily metabolic load of benzyl alcohol from these combined sources (see PRECAUTIONS: Pediatric Use).

Rare instances of anaphylaxis have occurred in patients receiving corticosteroid therapy (see ADVERSE REACTIONS). Cases of serious anaphylaxis, including death, have been reported in individuals receiving triamcinolone acetonide injection, regardless of the route of administration.

Because triamcinolone acetonide injectable suspension is a suspension, it should notbe administered intravenously.

Unless a deepintramuscular injection is given, local atrophy is likely to occur (for recommendations on injection techniques, see DOSAGE AND ADMINISTRATION). Due to the significantly higher incidence of local atrophy when the material is injected into the deltoid area, this injection site should be avoided in favor of the gluteal area.

Increased dosage of rapidly acting corticosteroids is indicated in patients on corticosteroid therapy subjected to any unusual stress before, during, and after the stressful situation. Triamcinolone acetonide injectable suspension is a long-acting preparation, and is not suitable for use in acute stress situations. To avoid drug-induced adrenal insufficiency, supportive dosage may be required in times of stress (such as trauma, surgery, or severe illness) both during treatment with triamcinolone acetonide injectable suspension and for a year afterwards.

Results from one multicenter, randomized, placebo-controlled study with methylprednisolone hemisuccinate, an intravenous corticosteroid, showed an increase in early (at 2 weeks) and late (at 6 months) mortality in patients with cranial trauma who were determined not to have other clear indications for corticosteroid treatment. High doses of systemic corticosteroids, including triamcinolone acetonide injectable suspension should not be used for the treatment of traumatic brain injury.

Cardio-Renal

Average and large doses of corticosteroids can cause elevation of blood pressure, salt and water retention and increased excretion of potassium. These effects are less likely to occur with the synthetic derivatives except when they are used in large doses. Dietary salt restriction and potassium supplementation may be necessary (see PRECAUTIONS). All corticosteroids increase calcium excretion.

Literature reports suggest an apparent association between use of corticosteroids and left ventricular free wall rupture after a recent myocardial infarction; therefore, therapy with corticosteroids should be used with great caution in these patients.

Endocrine

Corticosteroids can produce reversible hypothalamic-pituitary-adrenal (HPA) axis suppression with the potential for glucocorticosteroid insufficiency after withdrawal of treatment.

Metabolic clearance of corticosteroids is decreased in hypothyroid patients and increased in hyperthyroid patients. Changes in thyroid status of the patient may necessitate adjustment in dosage.

Infections

General

Patients who are on corticosteroids are more susceptible to infections than are healthy individuals. There may be decreased resistance and inability to localize infection when corticosteroids are used. Infection with any pathogen (viral, bacterial, fungal, protozoan, or helminthic) in any location of the body may be associated with the use of corticosteroids alone or in combination with other immunosuppressive agents. These infections may be mild to severe. With increasing doses of corticosteroids, the rate of occurrence of infectious complications increases. Corticosteroids may also mask some signs of current infection.

Fungal Infections

Corticosteroids may exacerbate systemic fungal infections and therefore should not be used in the presence of such infections unless they are needed to control drug reactions. There have been cases reported in which concomitant use of amphotericin B and hydrocortisone was followed by cardiac enlargement and congestive heart failure (see PRECAUTIONS: Drug Interactions: Amphotericin B injection and potassium-depleting agents).

Special Pathogens

Latent disease may be activated or there may be an exacerbation of intercurrent infections due to pathogens, including those caused by Amoeba, Candida, Cryptococcus, Mycobacterium, Nocardia, Pneumocystis,or Toxoplasma.

It is recommended that latent amebiasis or active amebiasis be ruled out before initiating corticosteroid therapy in any patient who has spent time in the tropics or in any patient with unexplained diarrhea.

Similarly, corticosteroids should be used with great care in patients with known or suspected Strongyloides(threadworm) infestation. In such patients, corticosteroid-induced immunosuppression may lead to Strongyloideshyperinfection and dissemination with widespread larval migration, often accompanied by severe enterocolitis and potentially fatal gram-negative septicemia.

Corticosteroids should not be used in cerebral malaria.

Tuberculosis

The use of corticosteroids in patients with active tuberculosis should be restricted to those cases of fulminating or disseminated tuberculosis in which the corticosteroid is used for the management of the disease in conjunction with an appropriate anti-tuberculosis regimen. If corticosteroids are indicated in patients with latent tuberculosis or tuberculin reactivity, close observation is necessary as reactivation of the disease may occur. During prolonged corticosteroid therapy, these patients should receive chemoprophylaxis.

Vaccination

Administration of live or live, attenuated vaccines is contraindicated in patients receiving immunosuppressive doses of corticosteroids. Killed or inactivated vaccines may be administered. However, the response to such vaccines cannot be predicted.Immunization procedures may be undertaken in patients who are receiving corticosteroids as replacement therapy, e.g., for Addison’s disease.

Viral Infections

Chicken pox and measles can have a more serious or even fatal course in pediatric and adult patients on corticosteroids. In pediatric and adult patients who have not had these diseases, particular care should be taken to avoid exposure. The contribution of the underlying disease and/or prior corticosteroid treatment to the risk is also not known. If exposed to chicken pox, prophylaxis with varicella zoster immune globulin (VZIG) may be indicated. If exposed to measles, prophylaxis with immunoglobulin (IG) may be indicated (see the respective package inserts for complete VZIG and IG prescribing information). If chicken pox develops, treatment with antiviral agents should be considered.

Neurologic

Epidural and intrathecal administration of this product is not recommended. Reports of serious medical events, including death, have been associated with epidural and intrathecal routes of corticosteroid administration (see ADVERSE REACTIONS: Gastrointestinaland Neurologic/Psychiatric).

Ophthalmic

Use of corticosteroids may produce posterior subcapsular cataracts, glaucoma with possible damage to the optic nerves, and may enhance the establishment of secondary ocular infections due to bacteria, fungi, or viruses. The use of oral corticosteroids is not recommended in the treatment of optic neuritis and may lead to an increase in the risk of new episodes. Corticosteroids should not be used in active ocular herpes simplex.

Adequate studies to demonstrate the safety of triamcinolone acetonide injectable suspension use by intraturbinal, subconjunctival, sub-Tenons, retrobulbar and intraocular (intravitreal) injections have not been performed. Endophthalmitis, eye inflammation, increased intraocular pressure and visual disturbances including vision loss have been reported with intravitreal administration. Administration of triamcinolone acetonide injectable suspension intraocularly or into the nasal turbinates is not recommended.

Intraocular injection of corticosteroid formulations containing benzyl alcohol, such as triamcinolone acetonide injectable suspension is not recommended because of potential toxicity from the benzyl alcohol.

PRECAUTIONS

General

This product, like many other steroid formulations, is sensitive to heat. Therefore, it should not be autoclaved when it is desirable to sterilize the exterior of the vial.

The lowest possible dose of corticosteroid should be used to control the condition under treatment. When reduction in dosage is possible, the reduction should be gradual.

Since complications of treatment with glucocorticoids are dependent on the size of the dose and the duration of treatment, a risk/benefit decision must be made in each individual case as to dose and duration of treatment and as to whether daily or intermittent therapy should be used.

Kaposi’s sarcoma has been reported to occur in patients receiving corticosteroid therapy, most often for chronic conditions. Discontinuation of corticosteroids may result in clinical improvement.

Cardio-Renal

As sodium retention with resultant edema and potassium loss may occur in patients receiving corticosteroids, these agents should be used with caution in patients with congestive heart failure, hypertension, or renal insufficiency.

Endocrine

Drug-induced secondary adrenocortical insufficiency may be minimized by gradual reduction of dosage. This type of relative insufficiency may persist for months after discontinuation of therapy; therefore, in any situation of stress occurring during that period, hormone therapy should be reinstituted. Since mineralocorticoid secretion may be impaired, salt and/or a mineralocorticoid should be administered concurrently.

Gastrointestinal

Steroids should be used with caution in active or latent peptic ulcers, diverticulitis, fresh intestinal anastomoses and nonspecific ulcerative colitis, since they may increase the risk of a perforation.

Signs of peritoneal irritation following gastrointestinal perforation in patients receiving corticosteroids may be minimal or absent.

There is an enhanced effect of corticosteroids in patients with cirrhosis.

Intra-Articular and Soft Tissue Administration

Intra-articularly injected corticosteroids may be systemically absorbed.

Appropriate examination of any joint fluid present is necessary to exclude a septic process.

A marked increase in pain accompanied by local swelling, further restriction of joint motion, fever and malaise are suggestive of septic arthritis. If this complication occurs and the diagnosis of sepsis is confirmed, appropriate antimicrobial therapy should be instituted.

Injection of a steroid into an infected site is to be avoided. Local injection of a steroid into a previously infected joint is not usually recommended.

Corticosteroid injection into unstable joints is generally not recommended.

Intra-articular injection may result in damage to joint tissues (see ADVERSE REACTIONS: Musculoskeletal).

Musculoskeletal

Corticosteroids decrease bone formation and increase bone resorption both through their effect on calcium regulation (i.e. decreasing absorption and increasing excretion) and inhibition of osteoblast function. This, together with a decrease in the protein matrix of the bone secondary to an increase in protein catabolism, and reduced sex hormone production, may lead to inhibition of bone growth in pediatric patients and the development of osteoporosis at any age. Special consideration should be given to patients at increased risk of osteoporosis (i.e. postmenopausal women) before initiating corticosteroid therapy.

Neuro-Psychiatric

Although controlled clinical trials have shown corticosteroids to be effective in speeding the resolution of acute exacerbations of multiple sclerosis, they do not show that they affect the ultimate outcome or natural history of the disease. The studies do show that relatively high doses of corticosteroids are necessary to demonstrate a significant effect (see DOSAGE AND ADMINISTRATION).

An acute myopathy has been observed with the use of high doses of corticosteroids, most often occurring in patients with disorders of neuromuscular transmission (e.g., myasthenia gravis), or in patients receiving concomitant therapy with neuromuscular blocking drugs (e.g., pancuronium). This acute myopathy is generalized, may involve ocular and respiratory muscles, and may result in quadriparesis. Elevation of creatinine kinase may occur. Clinical improvement or recovery after stopping corticosteroids may require weeks to years.

Psychiatric derangements may appear when corticosteroids are used, ranging from euphoria, insomnia, mood swings, personality changes and severe depression to frank psychotic manifestations. Also, existing emotional instability or psychotic tendencies may be aggravated by corticosteroids.

Ophthalmic

Intraocular pressure may become elevated in some individuals. If steroid therapy is continued for more than 6 weeks, intraocular pressure should be monitored.

Information for Patients

Patients should be warned not to discontinue the use of corticosteroids abruptly or without medical supervision, to advise any medical attendants that they are taking corticosteroids, and to seek medical advice at once should they develop fever or other signs of infection.

Persons who are on corticosteroids should be warned to avoid exposure to chicken pox or measles. Patients should also be advised that if they are exposed, medical advice should be sought without delay.

Drug Interactions

Aminoglutethimide:Aminoglutethimide may lead to a loss of corticosteroid-induced adrenal suppression.

Amphotericin B injection and potassium-depleting agents:When corticosteroids are administered concomitantly with potassium-depleting agents (i.e. amphotericin B, diuretics), patients should be observed closely for development of hypokalemia. There have been cases reported in which concomitant use of amphotericin B and hydrocortisone was followed by cardiac enlargement and congestive heart failure.

Antibiotics:Macrolide antibiotics have been reported to cause a significant decrease in corticosteroid clearance.

Anticholinesterases:Concomitant use of anticholinesterase agents and corticosteroids may produce severe weakness in patients with myasthenia gravis. If possible, anticholinesterase agents should be withdrawn at least 24 hours before initiating corticosteroid therapy.

Anticoagulants, oral:Co-administration of corticosteroids and warfarin usually results in inhibition of response to warfarin, although there have been some conflicting reports. Therefore, coagulation indices should be monitored frequently to maintain the desired anticoagulant effect.

Antidiabetics:Because corticosteroids may increase blood glucose concentrations, dosage adjustments of antidiabetic agents may be required.

Antitubercular drugs:Serum concentrations of isoniazid may be decreased.

Cholestyramine:Cholestyramine may increase the clearance of corticosteroids.

Cyclosporine:Increased activity of both cyclosporine and corticosteroids may occur when the two are used concurrently. Convulsions have been reported with this concurrent use.

CYP 3A4 inhibitors:Triamcinolone acetonide is a substrate of CYP3A4. Ketoconazole has been reported to decrease the metabolism of certain corticosteroids by up to 60%, leading to an increased risk of corticosteroid side effects. Co-administration of other strong CYP3A4 inhibitors (e.g., ritonavir, atazanavir, clarithromycin, indinavir, itraconazole, nefazodone, nelfinavir, saquinavir, telithromycin, cobicistat-containing products) with triamcinolone acetonide injectable suspension may cause increased plasma concentration of triamcinolone leading to adverse reactions (see ADVERSE REACTIONS). During postmarketing use, there have been reports of clinically significant drug interactions in patients receiving triamcinolone acetonide and strong CYP3A4 inhibitors (e.g., ritonavir) (see WARNINGS, Endocrineand PRECAUTIONS, Endocrine). Consider the benefit-risk of concomitant use and monitor for systemic corticosteroid side effects.

Digitalis glycosides:Patients on digitalis glycosides may be at increased risk of arrhythmias due to hypokalemia.

Estrogens, including oral contraceptives:Estrogens may decrease the hepatic metabolism of certain corticosteroids, thereby increasing their effect.

Hepatic enzyme inducers (e.g., barbiturates, phenytoin, carbamazepine, rifampin):Drugs which induce hepatic microsomal drug metabolizing enzyme activity may enhance the metabolism of corticosteroids and require that the dosage of the corticosteroid be increased.

Nonsteroidal anti-inflammatory drugs (NSAIDs):Concomitant use of aspirin (or other nonsteroidal anti-inflammatory drugs) and corticosteroids increases the risk of gastrointestinal side effects. Aspirin should be used cautiously in conjunction with corticosteroids in hypoprothrombinemia. The clearance of salicylates may be increased with concurrent use of corticosteroids.

Skin tests:Corticosteroids may suppress reactions to skin tests.

Vaccines:Patients on prolonged corticosteroid therapy may exhibit a diminished response to toxoids and live or inactivated vaccines due to inhibition of antibody response. Corticosteroids may also potentiate the replication of some organisms contained in live attenuated vaccines. Routine administration of vaccines or toxoids should be deferred until corticosteroid therapy is discontinued if possible (see WARNINGS: Infections: Vaccination).

Carcinogenesis, Mutagenesis, Impairment of Fertility

No adequate studies have been conducted in animals to determine whether corticosteroids have a potential for carcinogenesis or mutagenesis.

Steroids may increase or decrease motility and number of spermatozoa in some patients.

Pregnancy

Teratogenic Effects

Corticosteroids have been shown to be teratogenic in many species when given in doses equivalent to the human dose. Animal studies in which corticosteroids have been given to pregnant mice, rats and rabbits have yielded an increased incidence of cleft palate in the offspring. There are no adequate and well-controlled studies in pregnant women. Corticosteroids should be used during pregnancy only if the potential benefit justifies the potential risk to the fetus. Infants born to mothers who have received corticosteroids during pregnancy should be carefully observed for signs of hypoadrenalism.

Nursing Mothers

Systemically administered corticosteroids appear in human milk and could suppress growth, interfere with endogenous corticosteroid production, or cause other untoward effects. Caution should be exercised when corticosteroids are administered to a nursing woman.

Pediatric Use

This product contains benzyl alcohol as a preservative. Benzyl alcohol, a component of this product, has been associated with serious adverse events and death, particularly in pediatric patients. The “gasping syndrome” (characterized by central nervous system depression, metabolic acidosis, gasping respirations and high levels of benzyl alcohol and its metabolites found in the blood and urine) has been associated with benzyl alcohol dosages > 99 mg/kg/day in neonates and low-birth-weight neonates. Additional symptoms may include gradual neurological deterioration, seizures, intracranial hemorrhage, hematologic abnormalities, skin breakdown, hepatic and renal failure, hypotension, bradycardia and cardiovascular collapse. Although normal therapeutic doses of this product deliver amounts of benzyl alcohol that are substantially lower than those reported in association with the “gasping syndrome,” the minimum amount of benzyl alcohol at which toxicity may occur is not known. Premature and low-birth-weight infants, as well as patients receiving high dosages, may be more likely to develop toxicity. Practitioners administering this and other medications containing benzyl alcohol should consider the combined daily metabolic load of benzyl alcohol from all sources.

The efficacy and safety of corticosteroids in the pediatric population are based on the well-established course of effect of corticosteroids which is similar in pediatric and adult populations. Published studies provide evidence of efficacy and safety in pediatric patients for the treatment of nephrotic syndrome (> 2 years of age), and aggressive lymphomas and leukemias (> 1 month of age). Other indications for pediatric use of corticosteroids, e.g., severe asthma and wheezing, are based on adequate and well-controlled trials conducted in adults, on the premises that the course of the diseases and their pathophysiology are considered to be substantially similar in both populations.

The adverse effects of corticosteroids in pediatric patients are similar to those in adults (see ADVERSE REACTIONS). Like adults, pediatric patients should be carefully observed with frequent measurements of blood pressure, weight, height, intraocular pressure and clinical evaluation for the presence of infection, psychosocial disturbances, thromboembolism, peptic ulcers, cataracts and osteoporosis. Pediatric patients who are treated with corticosteroids by any route, including systemically administered corticosteroids, may experience a decrease in their growth velocity. This negative impact of corticosteroids on growth has been observed at low systemic doses and in the absence of laboratory evidence of HPA axis suppression (i.e. cosyntropin stimulation and basal cortisol plasma levels). Growth velocity may therefore be a more sensitive indicator of systemic corticosteroid exposure in pediatric patients than some commonly used tests of HPA axis function. The linear growth of pediatric patients treated with corticosteroids should be monitored, and the potential growth effects of prolonged treatment should be weighed against clinical benefits obtained and the availability of treatment alternatives. In order to minimize the potential growth effects of corticosteroids, pediatric patients should be titratedto the lowest effective dose.

Geriatric Use

No overall differences in safety or effectiveness were observed between elderly subjects and younger subjects, and other reported clinical experience has not identified differences in responses between the elderly and younger patients, but greater sensitivity of some older individuals cannot be ruled out.

ADVERSE REACTIONS

(listed alphabetically under each subsection)

The following adverse reactions may be associated with corticosteroid therapy:

Allergic reactions:Anaphylaxis including death, angioedema.

Cardiovascular:Bradycardia, cardiac arrest, cardiac arrhythmias, cardiac enlargement, circulatory collapse, congestive heart failure, fat embolism, hypertension, hypertrophic cardiomyopathy in premature infants, myocardial rupture following recent myocardial infarction (see WARNINGS), pulmonary edema, syncope, tachycardia, thromboembolism, thrombophlebitis, vasculitis.

Dermatologic:Acne, allergic dermatitis, cutaneous and subcutaneous atrophy, dry scaly skin, ecchymoses and petechiae, edema, erythema, hyperpigmentation, hypopigmentation, impaired wound healing, increased sweating, lupus erythematosus-like lesions, purpura, rash, sterile abscess, striae, suppressed reactions to skin tests, thin fragile skin, thinning scalp hair, urticaria.

Endocrine:Decreased carbohydrate and glucose tolerance, development of cushingoid state, glycosuria, hirsutism, hypertrichosis, increased requirements for insulin or oral hypoglycemic agents in diabetes, manifestations of latent diabetes mellitus, menstrual irregularities, postmenopausal vaginal hemorrhage, secondary adrenocortical and pituitary unresponsiveness (particularly in times of stress, as in trauma, surgery, or illness), suppression of growth in pediatric patients.

Fluid and electrolyte disturbances:Congestive heart failure in susceptible patients, fluid retention, hypokalemic alkalosis, potassium loss, sodium retention.

Gastrointestinal:Abdominal distention, bowel/bladder dysfunction (after intrathecal administration [see WARNINGS: Neurologic]), elevation in serum liver enzyme levels (usually reversible upon discontinuation), hepatomegaly, increased appetite, nausea, pancreatitis, peptic ulcer with possible perforation and hemorrhage, perforation of the small and large intestine (particularly in patients with inflammatory bowel disease), ulcerative esophagitis.

Metabolic:Negative nitrogen balance due to protein catabolism.

Musculoskeletal:Aseptic necrosis of femoral and humeral heads, calcinosis (following intra-articular or intralesional use), Charcot-like arthropathy, loss of muscle mass, muscle weakness, osteoporosis, pathologic fracture of long bones, post injection flare (following intra-articular use), steroid myopathy, tendon rupture, vertebral compression fractures.

Neurologic/Psychiatric:Convulsions, depression, emotional instability, euphoria, headache, increased intracranial pressure with papilledema (pseudotumor cerebri) usually following discontinuation of treatment, insomnia, mood swings, neuritis, neuropathy, paresthesia, personality changes, psychiatric disorders, vertigo. Arachnoiditis, meningitis, paraparesis/paraplegia and sensory disturbances have occurred after intrathecal administration. Spinal cord infarction, paraplegia, quadriplegia, cortical blindness and stroke (including brainstem) have been reported after epidural administration of corticosteroids (see WARNINGS: Serious Neurologic Adverse Reactions with Epidural Administrationand WARNINGS: Neurologic).

Ophthalmic:Exophthalmos, glaucoma, increased intraocular pressure, posterior subcapsular cataracts, rare instances of blindness associated with periocular injections.

Other:Abnormal fat deposits, decreased resistance to infection, hiccups, increased or decreased motility and number of spermatozoa, malaise, moon face, weight gain.

To report SUSPECTED ADVERSE REACTIONS, contact Amneal Pharmaceuticals at 1-877-835-5472 or FDA at 1-800-FDA-1088 or www.fda.gov/medwatch.

OVERDOSAGE

Treatment of acute overdosage is by supportive and symptomatic therapy. For chronic overdosage in the face of severe disease requiring continuous steroid therapy, the dosage of the corticosteroid may be reduced only temporarily, or alternate day treatment may be introduced.

DOSAGE AND ADMINISTRATION

General

NOTE: CONTAINS BENZYL ALCOHOL (see PRECAUTIONS).

The initial dose of triamcinolone acetonide injectable suspension may vary from 2.5 mg to 100 mg per day depending on the specific disease entity being treated (see Dosagesection below). However, in certain overwhelming, acute, life-threatening situations, administration in dosages exceeding the usual dosages may be justified and may be in multiples of the oral dosages.

IT SHOULD BE EMPHASIZED THAT DOSAGE REQUIREMENTS ARE VARIABLE AND MUST BE INDIVIDUALIZED ON THE BASIS OF THE DISEASE UNDER TREATMENT AND THE RESPONSE OF THE PATIENT.After a favorable response is noted, the proper maintenance dosage should be determined by decreasing the initial drug dosage in small decrements at appropriate time intervals until the lowest dosage which will maintain an adequate clinical response is reached. Situations which may make dosage adjustments necessary are changes in clinical status secondary to remissions or exacerbations in the disease process, the patient’s individual drug responsiveness, and the effect of patient exposure to stressful situations not directly related to the disease entity under treatment. In this latter situation it may be necessary to increase the dosage of the corticosteroid for a period of time consistent with the patient’s condition. If after long-term therapy the drug is to be stopped, it is recommended that it be withdrawn gradually rather than abruptly.

Dosage

SYSTEMIC

The suggested initial dose is 60 mg, injected deeply into the gluteal muscle. Atrophy of subcutaneous fat may occur if the injection is not properly given. Dosage is usually adjusted within the range of 40 mg to 80 mg, depending upon patient response and duration of relief. However, some patients may be well controlled on doses as low as 20 mg or less.

Hay fever or pollen asthma: Patients with hay fever or pollen asthma who are not responding to pollen administration and other conventional therapy may obtain a remission of symptoms lasting throughout the pollen season after a single injection of 40 mg to 100 mg.

In the treatment of acute exacerbations of multiple sclerosis, daily doses of 160 mg of triamcinolone for a week followed by 64 mg every other day for one month are recommended (see PRECAUTIONS: Neuro-Psychiatric).

In pediatric patients, the initial dose of triamcinolone may vary depending on the specific disease entity being treated. The range of initial doses is 0.11 to 1.6 mg/kg/day in 3 or 4 divided doses (3.2 to 48 mg/m^2bsa/day).

For the purpose of comparison, the following is the equivalent milligram dosage of the various glucocorticoids:

Cortisone, 25 | Triamcinolone, 4
Hydrocortisone, 20 | Paramethasone, 2
Prednisolone, 5 | Betamethasone, 0.75
Prednisone, 5 | Dexamethasone, 0.75
Methylprednisolone, 4

These dose relationships apply only to oral or intravenous administration of these compounds. When these substances or their derivatives are injected intramuscularly or into joint spaces, their relative properties may be greatly altered.

LOCAL

Intra-articular administration:A single local injection of triamcinolone acetonide is frequently sufficient, but several injections may be needed for adequate relief of symptoms.

Initial dose:2.5 mg to 5 mg for smaller joints and from 5 mg to 15 mg for larger joints, depending on the specific disease entity being treated. For adults, doses up to 10 mg for smaller areas and up to 40 mg for larger areas have usually been sufficient. Single injections into several joints, up to a total of 80 mg, have been given.

Administration

GENERAL

STRICT ASEPTIC TECHNIQUE IS MANDATORY.The vial should be shaken before use to ensure a uniform suspension. Prior to withdrawal, the suspension should be inspected for clumping or granular appearance (agglomeration). An agglomerated product results from exposure to freezing temperatures and should not be used. After withdrawal, triamcinolone acetonide injectable suspension should be injected without delay to prevent settling in the syringe. Careful technique should be employed to avoid the possibility of entering a blood vessel or introducing infection.

SYSTEMIC

For systemic therapy, injection should be made deeply into the gluteal muscle(see WARNINGS). For adults, a minimum needle length of 1½ inches is recommended. In obese patients, a longer needle may be required. Use alternative sites for subsequent injections.

LOCAL

For treatment of joints, the usual intra-articular injection technique should be followed. If an excessive amount of synovial fluid is present in the joint, some, but not all, should be aspirated to aid in the relief of pain and to prevent undue dilution of the steroid.

With intra-articular administration, prior use of a local anesthetic may often be desirable. Care should be taken with this kind of injection, particularly in the deltoid region, to avoid injecting the suspension into the tissues surrounding the site, since this may lead to tissue atrophy.

In treating acute nonspecific tenosynovitis, care should be taken to ensure that the injection of the corticosteroid is made into the tendon sheath rather than the tendon substance. Epicondylitis may be treated by infiltrating the preparation into the area of greatest tenderness.

HOW SUPPLIED

Triamcinolone Acetonide Injectable Suspension, USP is supplied in vials providing 40 mg triamcinolone acetonide per mL.

40 mg/mL, 1 mL

1 mL single-dose vial: NDC 70121-1049-1

25 single-dose vials in 1 carton: NDC 70121-1049-5

Storage

Store at 20° to 25°C (68° to 77°F) [see USP Controlled Room Temperature].Protect from temperatures below 20°C (68°F). Store vial in carton to protect from light. Store vial upright.

Discard unused portions of single-dose vials.

Manufactured by:

Amneal Pharmaceuticals Pvt. Ltd.

Parenteral Unit

Ahmedabad 382213, INDIA

Distributed by:

Amneal Pharmaceuticals LLC

Bridgewater, NJ 08807

Rev. 08-2020-05

Povidine Iodine Swab

Active Ingredient Purpose

Povidone Iodine 10% v/v Antiseptic

Uses:

Section Text

- First aid antiseptic to help prevent skin infection in minor cuts, scrapes and burns.
- For preparation of the skin prior to surgery.
- Helps reduce bacteria that can potentially cause skin infections.

Warnings:

Section Text

- FOR EXTERNAL USE ONLY

Do not use:

- As a first aid antiseptic for more than 1 week.
- In the eyes.
- Over large areas of the body.

Ask a doctor before use if you have:

- Deep puncture wounds
- Animal bites
- Serious burns

Stop Use:

- If irritation and redness develop
- If condition persists for more than 72 hours, consult a physician.

Keep out of reach of children.If swallowed, get medical help or contact a Poison Control Center.

Directions Povidone iodine:

Tear at notch, remove applicator, use only once.

As a first aid antiseptic

- clean affected area
- apply 1 to 3 times daily
- may be covered with a sterile bandage, if bandaged let dry.

For preoperative patient skin preparation

- clean area
- apply to operative site prior to surgery using the applicator

Other information:

Store at room temperature.

Avoid excessive heat

INDICATIONS AND USAGE

For use as an

- first aid antiseptic
- pre-operative skin preperation

Inactive Ingredients

Inactive ingredients: nonoxynol-9, water

PACKAGE LABEL

NDC: 76420-720-01 Rx Only

Bupivilog Kit™

Kit Contains

1 Bupivacaine HCI 0.5% Single Dose Vial (10mL)

2 Triamcinolone Acetonide Injectable Suspension, USP 40 mg/mL(1mL)

1 Povidone-Iodine Swabsticks (3 Swabs)

1 Pair Nitrile Powder Free Sterile Gloves (M)

1 Drape

1 Adhesive Bandage

5 Non Sterile 4x4 Gauze

Needles and Syringes Not Included

1 Dose

Single Use Only

Distributed by
Enovachem™
PHARMACEUTICALS
Torrance, CA 90501